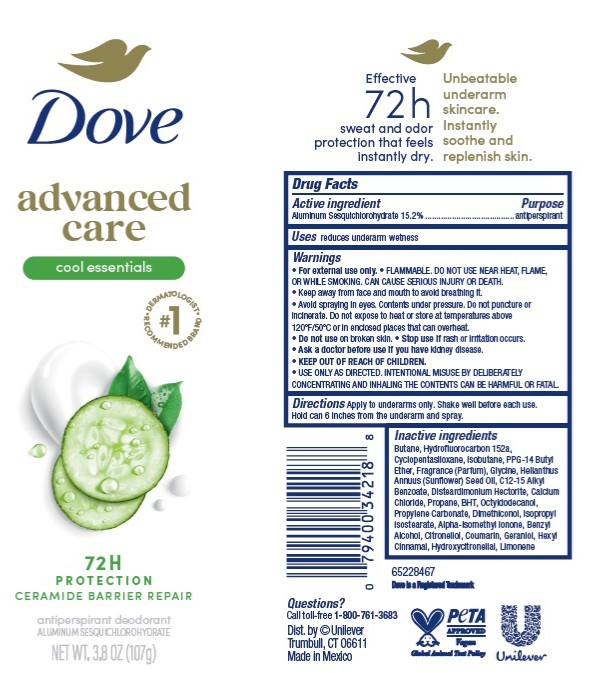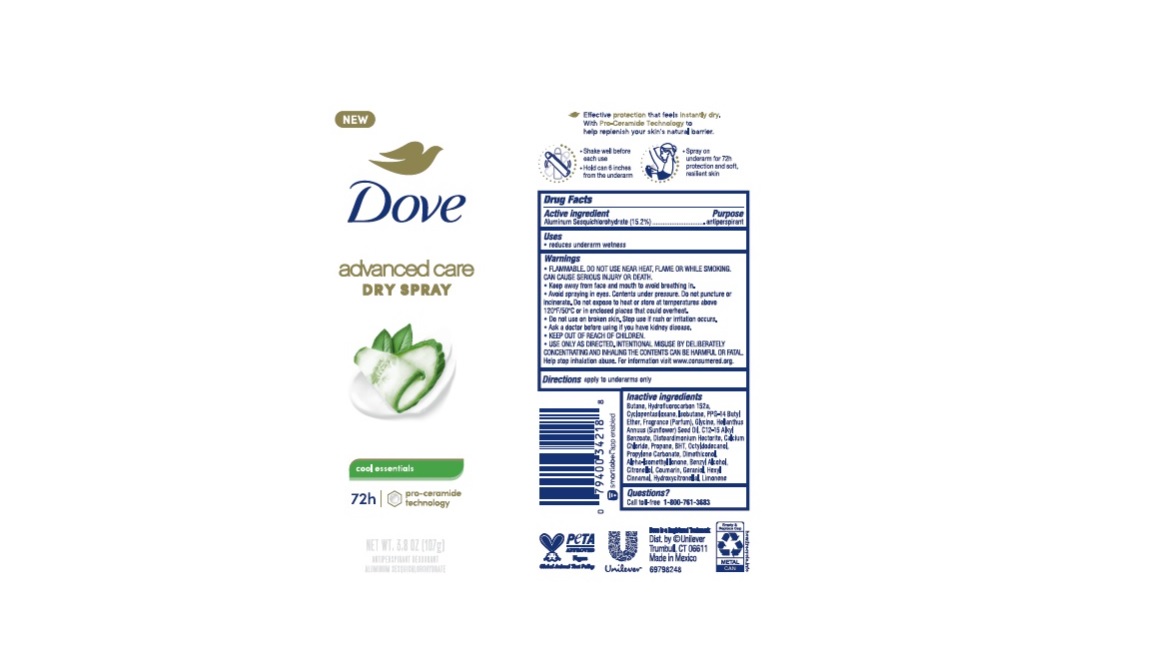 DRUG LABEL: Dove
NDC: 64942-2158 | Form: AEROSOL, SPRAY
Manufacturer: Conopco, Inc. d/b/a Unilever
Category: otc | Type: HUMAN OTC DRUG LABEL
Date: 20251219

ACTIVE INGREDIENTS: ALUMINUM SESQUICHLOROHYDRATE 15.2 g/100 g
INACTIVE INGREDIENTS: ISOBUTANE; PPG-14 BUTYL ETHER; SUNFLOWER OIL; DISTEARDIMONIUM HECTORITE; ALKYL (C12-15) BENZOATE; PROPANE; BUTYLATED HYDROXYTOLUENE; GERANIOL; ISOMETHYL-.ALPHA.-IONONE; HYDROXYCITRONELLAL; .ALPHA.-HEXYLCINNAMALDEHYDE; PROPYLENE CARBONATE; DIMETHICONOL (40 CST); OCTYLDODECANOL; BENZYL ALCOHOL; COUMARIN; CALCIUM CHLORIDE; 1,1-DIFLUOROETHANE; .BETA.-CITRONELLOL, (R)-; LIMONENE, (+)-; GLYCINE; BUTANE; CYCLOMETHICONE 5

Dove Advanced Care Cool Essentials Dry Spray 72h Antiperspirant Deodorant

Drug Facts

Active ingredient

Aluminum Sesquichlorohydrate (15.2)

Purpose

antiperspirant

Uses

reduces underarm wetness

Warnings

• FLAMMABLE. DO NOT USE NEAR HEAT, FLAME, OR WHILE SMOKING. CAN CAUSE SERIOUS INJURY OR DEATH
• Keep away from face and mouth to avoid breathing in.
• Avoid spraying in eyes. Contents under pressure. Do not puncture or incinerate. Do not expose to heat or store at temperatures above 120°F/50°C or in enclosed places that could overheat
• Do not use on broken skin. Stop use if rash or irritation occurs.
• Ask a doctor before using if you have kidney disease.
• USE ONLY AS DIRECTED. INTENTIONAL MISUSE BY DELIBERATELY CONCENTRATING AND INHALING THE CONTENTS CAN BE HARMFUL OR FATAL.
Help stop inhalation abuse. For information visit www.inhalant.org

• KEEP OUT OF REACH OF CHILDREN

Directions

apply to underarms only

Inactive ingredients

Butane, Hydrofluorocarbon 152a, Cyclopentasiloxane, Isobutane, PPG-14 Butyl Ether, Glycine, Fragrance (Parfum), Helianthus Annuus (Sunflower) Seed Oil, C12-15 Alkyl Benzoate, Disteardimonium Hectorite, Calcium Chloride, Propane, BHT, Octyldodecanol, Propylene Carbonate, Dimethiconol, Alpha-Isomethyl Ionone, Benzyl Alcohol, Citronellol, Coumarin, Geraniol, Hexyl Cinnamal, Hydroxycitronellal, Limonene

Questions?

Call toll-free 1-800-761-3683